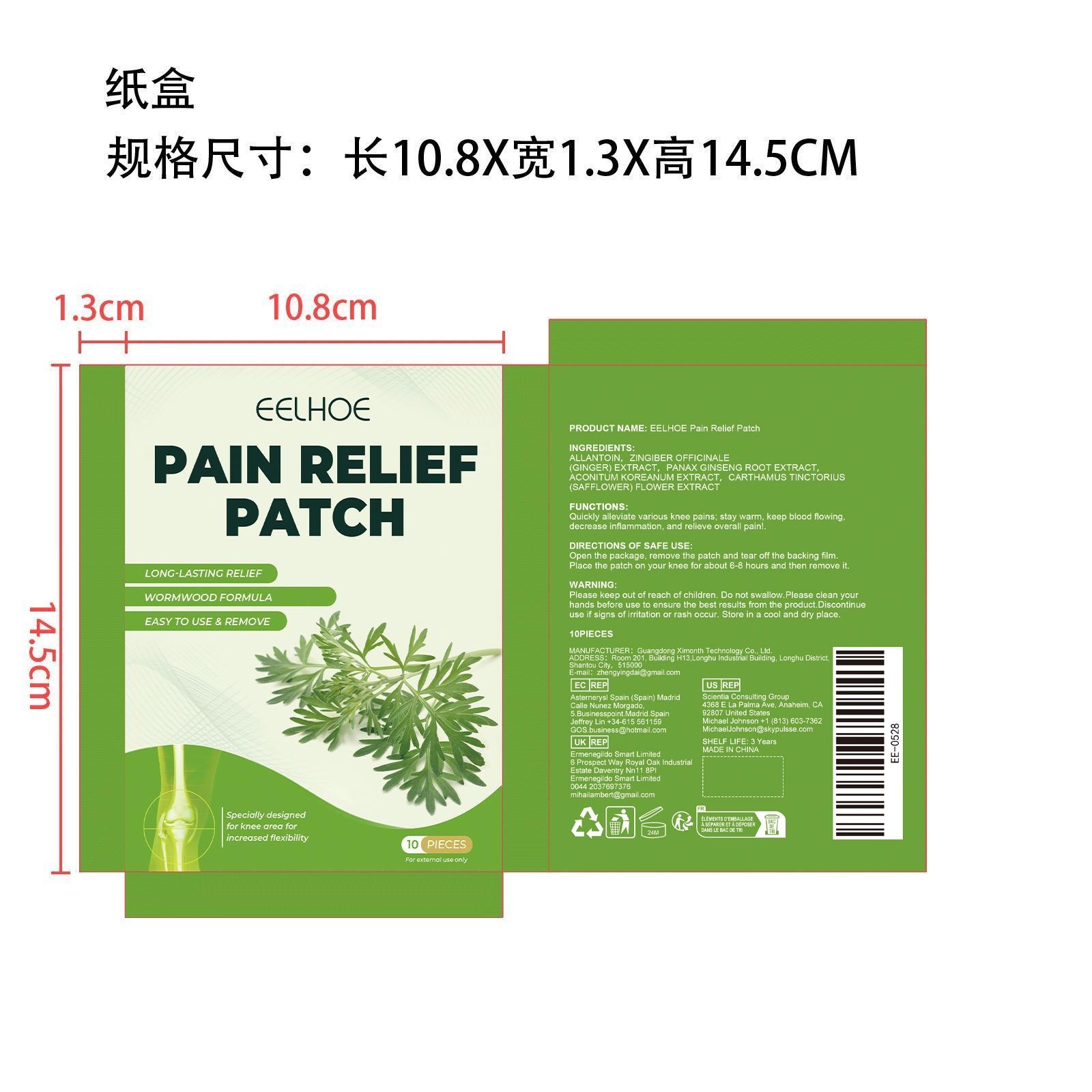 DRUG LABEL: EELHOE Pain Relief Patch
NDC: 84660-026 | Form: PATCH
Manufacturer: Guangdong Ximonth Technology Co., Ltd.
Category: otc | Type: HUMAN OTC DRUG LABEL
Date: 20240926

ACTIVE INGREDIENTS: ZINGIBER OFFICINALE WHOLE 9 g/36 g; ASIAN GINSENG 7.2 g/36 g; ACONITUM NAPELLUS ROOT 5.4 g/36 g; SAFFLOWER 3.6 g/36 g
INACTIVE INGREDIENTS: ALLANTOIN 10.8 g/36 g

Active Ingredient(s)

ZINGIBER OFFICINALE(GINGER) EXTRACT、PANAX GINSENG ROOT EXTRACT、ACONITUM KOREANUM EXTRACT、CARTHAMUS TINCTORIUS(SAFFLOWER) FLOWER EXTRACT

Purpose

Quickly alleviate various knee pains; stay warm, keep blood flowing, decrease inflammation, and relieve overall pain

Use

Open the package, remove the patch and tear off the backing film. Place the patch on your knee for about 6-8 hours and then remove it.

Warnings

Please keep out of reach of children.Do not swallow.Please clean your hands before use to ensure the best results from the product.Discontinue use if signs of irritation or rash occur.Store in a cool and dry place.

Do not use

Discontinue use if signs of irritation or rash occur

STOP USE

Discontinue use if signs of irritation or rash occur.

STORAGE AND HANDLING

Avoid freezing and excessive heat above 40C (104F) ）

Store in a cool and dry place.

KEEP OUT OF REACH OF CHILDREN

Please keep out of reach of children. Do not swallow.

INACTIVE INGREDIENT

ALLANTOIN